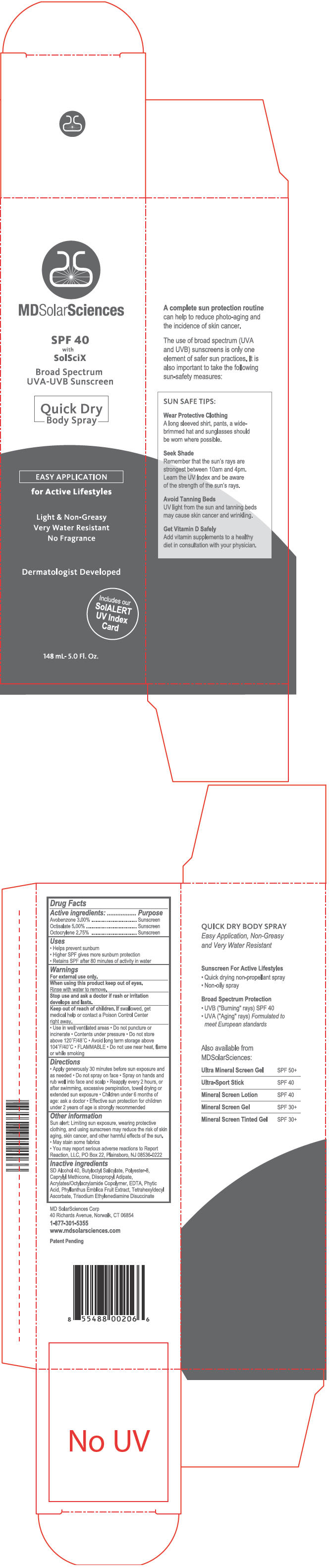 DRUG LABEL: MDSolarSciences 
NDC: 49358-544 | Form: SPRAY
Manufacturer: MD Solar Sciences
Category: otc | Type: HUMAN OTC DRUG LABEL
Date: 20120424

ACTIVE INGREDIENTS: Avobenzone 4.44 mL/148 mL; Octisalate 7.4 mL/148 mL; Octocrylene 4.07 mL/148 mL
INACTIVE INGREDIENTS: Butyloctyl Salicylate; Diisopropyl Adipate; Edetic Acid; Fytic Acid; Phyllanthus Emblica Fruit; Tetrahexyldecyl Ascorbate; Trisodium Ethylenediamine Disuccinate

SPF 40 Quick Dry Body Spray

Drug Facts

ACTIVE INGREDIENT

Active ingredients: | Purpose
Avobenzone 3.00% | Sunscreen
Octisalate 5.00% | Sunscreen
Octocrylene 2.75% | Sunscreen

Uses

- Helps prevent sunburn
- Higher SPF gives more sunburn protection
- Retains SPF after 80 minutes of activity in water

Warnings

For external use only.

When using this product keep out of eyes. Rinse with water to remove.

Stop use and ask a doctor if rash or irritation develops and lasts.

Keep out of reach of children. If swallowed, get medical help or contact Poison Control Center right away.

STORAGE AND HANDLING

- Use in well ventilated areas
- Do not puncture or incinerate
- Contents under pressure
- Do not store above 120°F/48°C
- Avoid long term storage above 104°F/40°C
- FLAMMABLE
- Do not use near heat, flame or while smoking

Directions

- Apply generously 30 minutes before sun exposure and as needed
- Do not spray on face
- Spray on hands and rub well into face and scalp
- Reapply every 2 hours, or after swimming, excessive perspiration, towel drying or extended sun exposure
- Children under 6 months of age: ask a doctor
- Effective sun protection for children under 2 years of age is strongly recommended

Other information

Sun alert: Limiting sun exposure, wearing protective clothing, and using sunscreen may reduce the risk of skin aging, skin cancer, and other harmful effects of the sun.

- May stain some fabrics
- You may report serious adverse reactions to Report Reaction, LLC, PO Box 22, Plainsboro, NJ 08536-0222

Inactive ingredients

SD Alcohol 40, Butyloctyl Salicylate, Polyester-8, Caprylyl Methicone, Diisopropyl Adipate, Acrylates/Octylacrylamide Copolymer, EDTA, Phytic Acid, Phyllanthus Emblica Fruit Extract, Tetrahexyldecyl Ascorbate, Trisodium Ethylenediamine Disuccinate

PRINCIPAL DISPLAY PANEL - 148 mL Can Carton

MDSolarSciences

SPF 40
with
SolSciX

Broad Spectrum
UVA-UVB Sunscreen

Quick Dry
Body Spray

EASY APPLICATION

for Active Lifestyles

Light & Non-Greasy
Very Water Resistant
No Fragrance

Dermatologist Developed

Includes our
SolALERT
UV Index
Card

148 mL- 5.0 Fl. Oz.